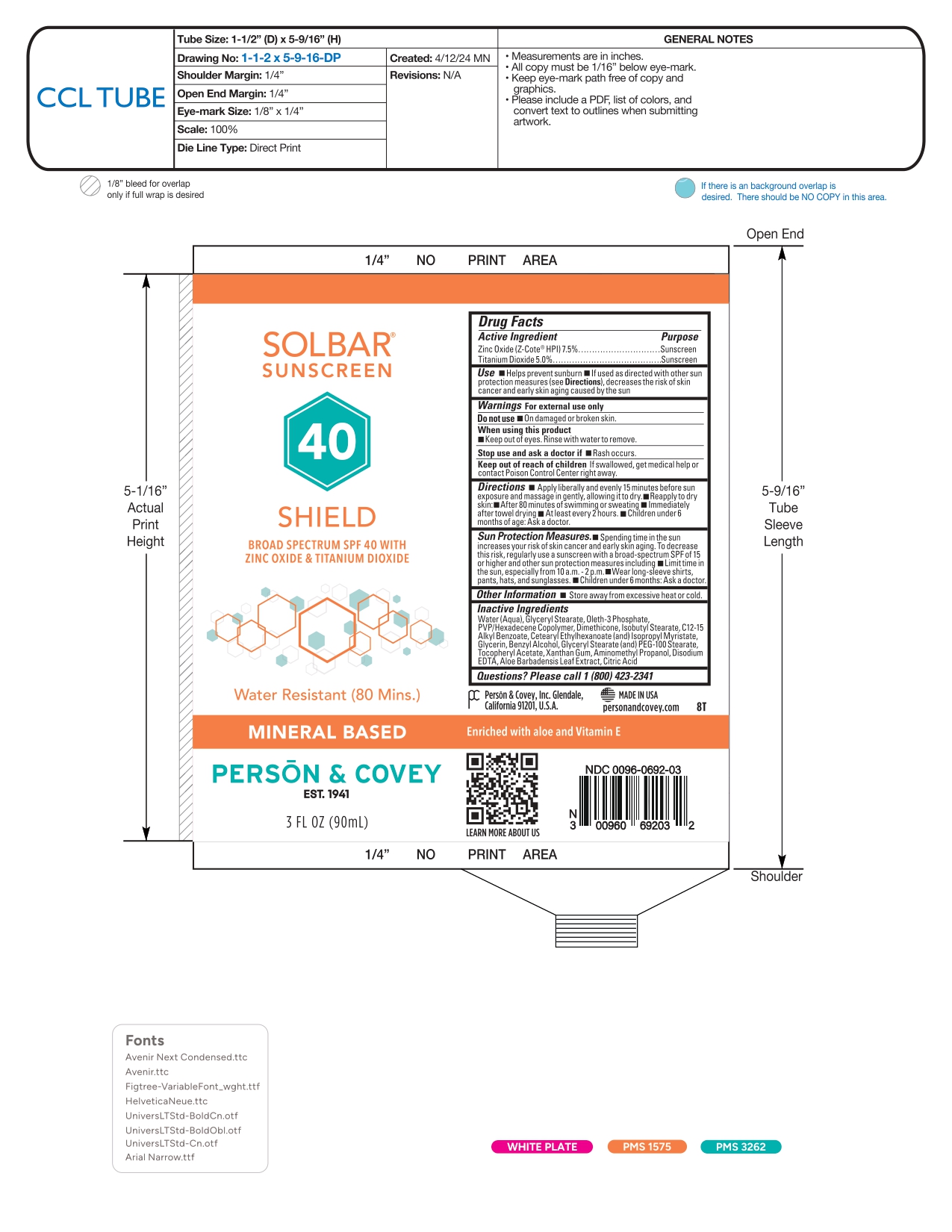 DRUG LABEL: SOLBAR SUNSCREEN 40 SHIELD
NDC: 0096-0692 | Form: CREAM
Manufacturer: Person and Covey
Category: otc | Type: HUMAN OTC DRUG LABEL
Date: 20260122

ACTIVE INGREDIENTS: ZINC OXIDE 75 mg/1 g; TITANIUM DIOXIDE 50 mg/1 g
INACTIVE INGREDIENTS: CETEARYL ETHYLHEXANOATE; ISOPROPYL MYRISTATE; C12-15 ALKYL BENZOATE; ALPHA-TOCOPHEROL ACETATE; XANTHAN GUM; AMINOMETHYL PROPANOL; CITRIC ACID; GLYCERYL MONOSTEARATE; EDETATE DISODIUM; ISOBUTYL STEARATE; DIMETHICONE; BENZYL ALCOHOL; ALOE BARBADENSIS LEAF JUICE; OLETH-3 PHOSPHATE; WATER; GLYCERIN; VP/HEXADECENE COPOLYMER; PEG-100 STEARATE

SOLBAR SHIELD - sunscreen cream

Active Ingredients

Zinc Oxide (Z-Cote® HPI) 7.5%

Titanium Dioxide 5.0%

Purpose

Sunscreen

Use

Helps prevent sunburn.
If used as directed with other sun protection measures (see Directions), decreases the risk of skin cancer and early skin aging caused by the sun.

Warnings

For external use only

Do not use on damaged or broken skin.

When using this product
Keep out of eyes. Rinse with water to remove.

Stop use and ask a doctor if rash occurs.

Keep out of reach of children

If swallowed, get medical help or a contact Poison Control Center right away.

Directions

- Apply liberally and evenly 15 minutes before sun exposure and massage in gently, allowing it to dry.
- Reapply to dry skin:
- After 80 minutes of swimming or sweating
- Immediately after towel drying
- At least every 2 hours.
- Children under 6 months of age: Ask a doctor.

Sun Protection Measures.
Spending time in the sun increases your risk of skin cancer and early skin aging. To decrease this risk, regularly use a sunscreen with a broad-spectrum SPF of 15 or higher and other sun protection measures including:
Limit time in the sun, especially from 10 a.m. - 2 p.m.
Wear long-sleeve shirts, pants, hats, and sunglasses.
Children under 6 months: Ask a doctor.

Other Information

Store away from excessive heat or cold.

Inactive Ingredients

Water (Aqua), Glyceryl Stearate, Oleth-3 Phosphate, PVP/Hexadecene Copolymer, Dimethicone, Isobutyl Stearate, C12-15 Alkyl Benzoate, Cetearyl Ethylhexanoate (and) Isopropyl Myristate, Glycerin, Benzyl Alcohol, Glyceryl Stearate (and) PEG-100 Stearate, Tocopheryl Acetate, Xanthan Gum, Aminomethyl Propanol, Disodium EDTA, Aloe Barbadensis Leaf Extract, Citric Acid

Questions? Please call 1 (800) 423-2341

Person & Covey, Inc. Glendale, California 91201, U.S.A.
MADE IN USA
personandcovey.com